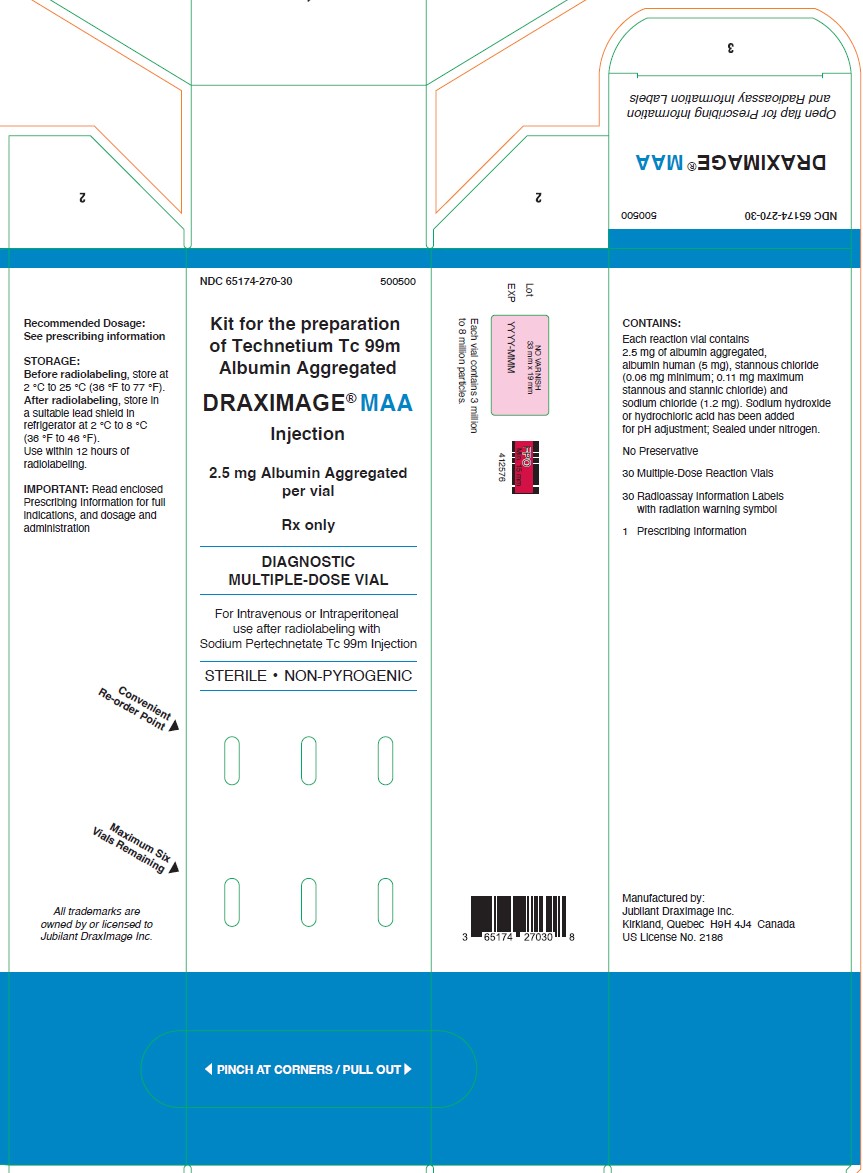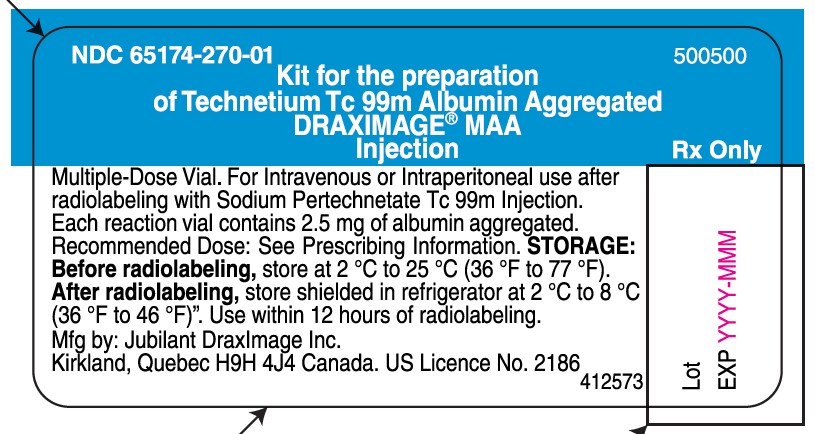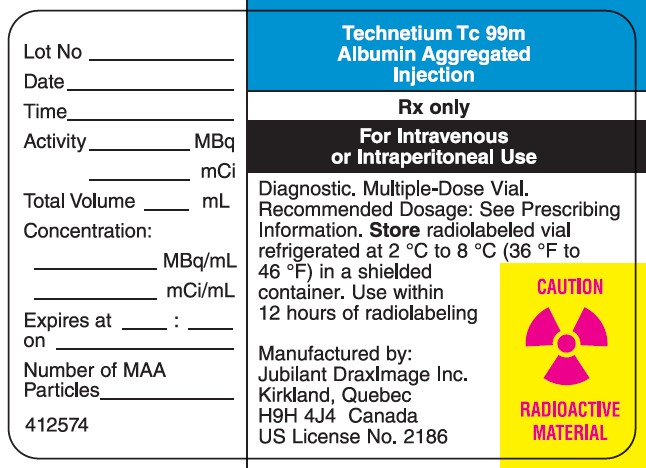 DRUG LABEL: DRAXIMAGE MAA
NDC: 65174-270 | Form: INJECTION, POWDER, FOR SOLUTION
Manufacturer: Jubilant DraxImage Inc
Category: prescription | Type: Human Prescription Drug Label
Date: 20240213

ACTIVE INGREDIENTS: ALBUMIN AGGREGATED 2.5 mg/1 1
INACTIVE INGREDIENTS: STANNOUS CHLORIDE 0.06 mg/1 1; ALBUMIN HUMAN 5 mg/1 1; SODIUM CHLORIDE 1.2 mg/1 1

HIGHLIGHTS OF PRESCRIBING INFORMATION

These highlights do not include all the information needed to use DRAXIMAGE® MAA safely and effectively. See full prescribing information for DRAXIMAGE MAA.
DRAXIMAGE MAA (kit for the preparation of technetium Tc 99m albumin aggregated) injection, for intravenous or intraperitoneal use
Initial U.S. Approval: 1987

1 INDICATIONS AND USAGE

DRAXIMAGE MAA, after radiolabeling with sodium pertechnetate Tc 99m, is a radioactive diagnostic agent indicated for:

- Lung scintigraphy as an adjunct in the evaluation of pulmonary perfusion in adults and pediatric patients. (1)
- Peritoneovenous shunt scintigraphy as an aid in the evaluation of its patency in adults.(1)

2 DOSAGE AND ADMINISTRATION

- For lung scintigraphy, the following recommended activity is administered by intravenous injection:
  - Adults: 37 MBq to 148 MBq (1 mCi to 4 mCi); 200,000 particles to 700,000 particles. (2.3)
  - Pediatric patients aged 4 weeks and older: 0.925 MBq/kg to 1.85 MBq/kg of body weight (0.025 mCi/kg to 0.05 mCi/kg); The minimum activity is 7.4 MBq (0.2 mCi). The number of particles will vary with age and body weight of the pediatric patient. (2.3)
  - Pediatric patients aged less than 4 weeks: 7.4 MBq to 18.5 MBq (0.2 mCi to 0.5 mCi); 10,000 particles to 50,000 particles. (2.3)
- For scintigraphy of peritoneovenous shunts in adults: 37 MBq to 111 MBq (1 mCi to 3 mCi); 200,000 particles to 700,000 particles by intraperitoneal injection. (2.4)
- See Full Prescribing Information for radiation safety, patient preparation, drug preparation, administration, imaging, and radiation dosimetry information. (2.1, 2.2, 2.5, 2.6, 2.7)

3 DOSAGE FORMS AND STRENGTHS

Kit for the preparation of Technetium Tc 99m Albumin Aggregated Injection: 2.5 mg of albumin aggregated as a lyophilized powder in a multiple-dose reaction vial. Upon radiolabeling, it provides a suspension of Technetium Tc 99m Albumin Aggregated Injection. Each vial contains 3,000,000 to 8,000,000 particles. (3)

4 CONTRAINDICATIONS

- Severe pulmonary hypertension. (4)
- A history of hypersensitivity reactions to albumin human.(4)

5 WARNINGS AND PRECAUTIONS

- Patients with Pulmonary Hypertension: Administer the lowest number of particles possible and have emergency resuscitation equipment available. (5.1)
- Hypersensitivity Reactions: Have emergency resuscitation equipment and trained personnel available. Interrupt the administration if a reaction occurs during administration. Monitor patients. (5.2)
- Risk of Temporary Impediment to Blood Flow in Patients with Right-to-Left Heart Shunts: Administer the lowest possible number of particles. (5.3)
- Radiation Risks: Ensure safe handling to minimize radiation exposure to the patient and healthcare providers. (5.4)

6 ADVERSE REACTIONS

The following adverse reactions have been reported: Death in patients with severe pulmonary hypertension, anaphylaxis, impairment of cardiac and circulatory functions in the form of changes in respiration, pulse, and blood pressure, chest pain, and possible syncope, urticaria, reddening of the face, sweating, nausea, and injection site reaction. (6)

To report SUSPECTED ADVERSE REACTIONS, contact Jubilant DraxImage Inc. at 1-888-633-5343 or FDA at 1-800-FDA-1088 or www.fda.gov/medwatch.

8 USE IN SPECIFIC POPULATIONS

Lactation: Temporarily discontinue breastfeeding. A lactating woman should pump and discard breastmilk for at least 24 hours after Technetium Tc 99m Albumin Aggregated Injection administration. (8.2)

FULL PRESCRIBING INFORMATION

1 INDICATIONS AND USAGE

DRAXIMAGE MAA, after radiolabeling with sodium pertechnetate Tc 99m, is indicated for:

- Lung scintigraphy as an adjunct in the evaluation of pulmonary perfusion in adults and pediatric patients.

- Peritoneovenous shunt scintigraphy as an aid in the evaluation of its patency in adult patients.

2 DOSAGE AND ADMINISTRATION

2.1 Radiation Safety – Drug Handling

After radiolabeling of DRAXIMAGE MAA, the vial contains Technetium Tc 99m Albumin Aggregated Injection. Handle Technetium Tc 99m Albumin Aggregated Injection with appropriate safety measures to minimize radiation exposure [see Warnings and Precautions (5.4)]. Use waterproof gloves, effective radiation shielding, and other appropriate safety measures when preparing and handling Technetium Tc 99m Albumin Aggregated Injection.

Radiopharmaceuticals should be used by or under the control of healthcare providers who are qualified by specific training and experience in the safe use and handling of radionuclides, and whose experience and training have been approved by the appropriate governmental agency authorized to license the use of radionuclides.

2.2 Patient Preparation

Instruct patients to drink a sufficient amount of water to ensure adequate hydration prior to administration of Technetium Tc 99m Albumin Aggregated Injection and to continue to drink and void frequently following administration to reduce radiation exposure [see Warnings and Precautions (5.4)].

2.3 Recommended Dosage for Lung Perfusion Scintigraphy

Adult Patients

The recommended activity for lung perfusion scintigraphy in adult patients is 37 MBq to 148 MBq (1 mCi to 4 mCi) by intravenous injection.

The number of particles per single injection should be 200,000 to 700,000 with the recommended number being approximately 350,000. Depending on the activity added and volume of the final radiolabeled product, the volume of the dose may vary from 0.2 mL to 1.9 mL.

The number of particles available per dose of Technetium Tc 99m Albumin Aggregated Injection will vary depending on the physical decay of the technetium-99m that has occurred. The number of particles in any dose and volume to be administered may be calculated as follows:

Va = D and P = Va x N

C x Fr VTc

Where:

Va = Volume to be administered in mL

D = Desired activity to be administered in MBq (mCi)

C = Concentration at calibration time of Sodium Pertechnetate Tc 99m Injection to be added to the reaction vial in MBq/mL (mCi/mL)

Fr = Fraction of technetium-99m remaining after the time of calibration from Table 7 [see Description (11.3)]

P = Number of particles in dose to be administered

Va = Volume to be administered in mL

VTc = Volume of Sodium Pertechnetate Tc 99m Injection added to reaction vial in mL

N = Number of particles per vial. The number of particles per vial for each lot is shipped with the product.

Pediatric Patients Aged 4 Weeks and Older

The recommended activity for lung perfusion scintigraphy in pediatric patients aged 4 weeks and older by intravenous injection is based on body weight and ranges from 0.925 MBq/kg to 1.85 MBq/kg (0.025 mCi/kg to 0.05 mCi/kg). The minimum recommended activity for lung perfusion scintigraphy in this age group is 7.4 MBq (0.2 mCi).

The number of particles will vary with age and body weight of the pediatric patient. Particle numbers administered in four different age and weight categories are provided in Table 1.

Table 1. Particle Numbers Administered in Four Different Age and Weight Categories of Pediatric Patients Receiving Maximum Recommended Activity of Technetium Tc 99m Albumin Aggregated Injection for Lung Perfusion Scintigraphy

Age | 15 years |  | 10 years |  |  | 5 years |  | 1 year
Weight (kg) | 55 |  | 33.5 |  |  | 20.3 |  | 12.1
Maximum recommended activity | MBq | mCi | MBq |  | mCi | MBq | mCi | MBq | mCi
Maximum recommended activity | 103.6 | 2.8 | 62.9 | 1.7 |  | 37 | 1 | 22.2 | 0.6
Range of particles administered | 200,000 to 700,000 |  | 200,000 to 300,000 |  |  | 200,000 to 300,000 |  | 50,000 to 150,000

Pediatric Patients Aged Less Than 4 Weeks (Neonates)

The recommended activity for lung perfusion scintigraphy in neonates by intravenous injection is 7.4 MBq to 18.5 MBq (0.2 mCi to 0.5 mCi). The number of particles in neonates for lung perfusion scintigraphy ranges from 10,000 to 50,000. Use the lowest possible number of particles for neonates.

2.4 Recommended Dosage for Peritoneovenous Shunt Scintigraphy in Adults

The recommended activity for peritoneovenous shunt scintigraphy in adult patients is 37 MBq to 111 MBq (1 mCi to 3 mCi) by intraperitoneal injection. The number of particles per single injection should be 200,000 to 700,000 with the recommended number being approximately 350,000. Depending on the activity added and volume of the final radiolabeled product, the volume of the dose may vary from 0.2 mL to 1.9 mL. For calculation of the number of particles to be administered, see Recommended Dosage for Lung Perfusion Scintigraphy in Adult Patients [see Dosage and Administration (2.3)]. Assure uniform mixing with peritoneal fluid.

Alternatively, administer the drug by percutaneous transtubal injection. The recommended activity for percutaneous transtubal (efferent limb) administration in adult patients is 12 MBq to 37 MBq (0.3 mCi to 1 mCi) in a volume not to exceed 0.5 mL.

2.5 Directions for Drug Preparation and Handling

Procedural Precautions

- Before radiolabeling, the contents of the kit are not radioactive. Contents of the vials are intended only for use in the preparation of Technetium Tc 99m Albumin Aggregated Injection and are NOT to be administered directly to the patient. After the Sodium Pertechnetate Tc 99m Injection is added, maintain adequate shielding of the radiolabeled product.
- Use aseptic procedures throughout and take precautions to minimize radiation exposure by use of suitable shielding.
- Wear waterproof gloves during the preparation procedure.
- Before radiolabeling a vial, inspect the vial for cracks and/or a melted plug or any other indication that the integrity of the vacuum seal has been lost.
- Use only oxidant-free Sodium Pertechnetate Tc 99m Injection to maintain the stannous ion in the reduced state.

Procedure for the Preparation of Technetium Tc 99m Albumin Aggregated Injection

1. Remove the protective cap from a reaction vial and swab the rubber septum with either an alcohol swab or a suitable bacteriostatic agent to disinfect the surface.
2. Place the vial in a suitable lead vial shield which has a fitted cap.
3. The maximum activity of Sodium Pertechnetate Tc 99m Injection to be added to a reaction vial varies with the number of particles per vial and is shown in Table 2. The number of particles per vial for each lot is shipped with the product. Calculate the amount of radioactivity per vial required to maintain the number of particles per dose within a recommended range while taking into account administered activity, radioactive decay and the number of patients [see Dosage and Administration (2.3,2.4)]. Other calculations for radiolabeling are permitted provided that the patient dose remains within the recommended range.
  Table 2. Maximum Activity of Sodium Pertechnetate Tc 99m Injection to be Added Based on Vial Particle Number
  Particles per vial | Maximum Activity of Sodium Pertechnetate Tc 99m Injection to be added per vial
  3 million to 4 million | 3.7 GBq (100 mCi)
  5 million | 4.44 GBq (120 mCi)
  6 million to 8 million | 6.85 GBq (185 mCi)
4. Using a shielded syringe, add the calculated amount of Sodium Pertechnetate Tc 99m Injection to the reaction vial aseptically.
5. Place the lead cap on the vial shield and mix the contents of the shielded vial by repeated gentle inversion until all the material is suspended. Do not shake to avoid formation of foam. To ensure maximum tagging, allow the preparation to stand for 15 minutes after mixing.
6. Using proper shielding, visually inspect the vial to ensure that the suspension is free of foreign matter before proceeding. Do not administer if foreign particulates are found in the preparation.
7. Assay the product in a suitable dose calibrator, record the radioassay information on the label with radiation warning symbol, and attach it to the vial shield.
8. No less than 90% of the sodium pertechnetate Tc 99m added to the reaction vial is bound to albumin aggregated at the time of preparation and remain bound throughout the usage lifetime of the preparation.

Storage and Handling of Technetium Tc 99m Albumin Aggregated Injection

- Store the radiolabeled product in the lead vial shield with cap in place during its in-use shelf life. Store the radiolabeled product refrigerated at 2 ºC to 8 ºC (36 ºF to 46 ºF) when not in use and use within 12 hours from the time of radiolabeling depending on the number of particles per vial, the activity added at radiolabeling and the final dose to be administered to the patient [see Dosage and Administration (2.3,2.4)].
- Technetium Tc 99m Albumin Aggregated Injection is physically unstable and consequently the particles settle with time. Failure to agitate the vial adequately before administration may result in non-uniform distribution of radioactive particles.
- Do not use if clumping of the contents is observed.
- Since the vials are sealed under an atmosphere of nitrogen to prevent oxidation of the complex, do not vent the vials. If repeated withdrawals are made from the vial, minimize replacement of the contents with air.
- Dispose unused Technetium Tc 99m Albumin Aggregated Injection in compliance with appropriate regulations.

2.6 Administration and Imaging Instructions

- Position the patient under the imaging apparatus before administration of Technetium Tc 99m Albumin Aggregated Injection because of rapid lung clearance of technetium Tc 99m albumin aggregated.
- Using proper shielding, visually inspect for foreign particulate matter and discoloration prior to administration. Do not administer if foreign particulates are found in the preparation.
- Mix the contents of the vial by gentle inversion just prior to withdrawing a patient dose.
- Withdraw the patient dose aseptically using a sterile needle (18 gauge to 21 gauge) and a shielded syringe.
- Measure the patient dose by a suitable radioactivity calibration system immediately prior to administration.
- Mix the contents of the syringe just before injection.
- Slow injection is recommended.
- If blood is drawn into the syringe, any unnecessary delay prior to injection may lead to clot formation.
- Begin lung imaging immediately after intravenous administration of Technetium Tc 99m Albumin Aggregated Injection. Due to high kidney uptake, imaging later than one-half hour after administration is not recommended.
- For peritoneovenous shunt imaging, obtain serial images of both the shunt and target organ.

2.7 Radiation Dosimetry

Intravenous Administration

Estimated radiation absorbed doses from intravenous administration are shown in Table 3.

Table 3. Estimated Radiation Absorbed Doses From Intravenous Administration of Technetium Tc 99m Albumin Aggregated Injection for Lung Perfusion Scintigraphy
Absorbed Dose per Activity Administered
(microGy/MBq)
Organs | Adults | 15 years | 10 years | 5 years | 1 year | Neonates
Total body | 4.05 | 3.96 | 7.63 | 8.38 | 13.5 | 32.4
Lungs | 59.5 | 74.3 | 138 | 157 | 297 | 1027
Liver | 4.86 | 11.6 | 28.6 | 16.8 | 27 | 75.7
Spleen | 4.59 | *-- | -- | -- | -- | --
Kidneys | 2.97 | -- | -- | -- | -- | --
Bladder Wall 2 hour void 4.8 hour void No voiding intervals | 8.11 14.9 -- | -- -- 39.6 | -- 62 -- | -- 83.8 -- | 67.6 -- -- | 114 -- --
Testes 2 hour void 4.8 hour void No voiding intervals | 1.62 1.76 -- | -- -- 3.47 | -- -- 3.18 | -- -- 5.14 | -- -- 5.86 | -- -- 16.8
Ovaries 2 hour void 4.8 hour void No voiding intervals | 2.03 2.3 -- | -- -- 3.96 | -- -- 7 | -- -- 5.14 | -- -- 9.01 | -- -- 20.5

*--: Not available

Intraperitoneal Administration

Estimated radiation absorbed doses from intraperitoneal administration are shown in Table 4.

Table 4. Estimated Radiation Absorbed Doses From Intraperitoneal Administration of Technetium Tc 99m Albumin Aggregated Injection for Peritoneovenous Shunt Scintigraphy in Adults
Absorbed Dose per Activity Administered
(microGy/MBq)
Organs | Shunt Patency (Open) | Shunt Patency (Closed)
Lung | 62.2 | 15.1
Ovaries or Testes | 1.62 to 2.7 | 15.1
Organ in the Peritoneal Cavity | *-- | 15.1
Total Body | 3.24 | 5.14

*--: Not available

3 DOSAGE FORMS AND STRENGTHS

Kit for the preparation of Technetium Tc 99m Albumin Aggregated Injection: 2.5 mg of albumin aggregated as a non-radioactive white lyophilized powder in a multiple-dose reaction vial for radiolabeling with Sodium Pertechnetate Tc 99m Injection to prepare a suspension of Technetium Tc 99m Albumin Aggregated Injection. Each vial contains 3,000,000 to 8,000,000 particles.

4 CONTRAINDICATIONS

DRAXIMAGE MAA is contraindicated in patients with:

- Severe pulmonary hypertension [see Warnings and Precautions (5.1)].
- A history of hypersensitivity to albumin human.Reactions have included anaphylaxis [see Warnings and Precautions (5.2)] .

5 WARNINGS AND PRECAUTIONS

5.1 Patients with Pulmonary Hypertension

Deaths have been reported in patients with severe pulmonary hypertension after the administration of technetium Tc 99m albumin aggregated products [see Adverse Reactions (6)].Assess patients for history or signs of pulmonary hypertension. DRAXIMAGE MAA is contraindicated in patients with severe pulmonary hypertension [see Contraindications (4)].Administer the lowest number of particles possible, have emergency resuscitation equipment available, and monitor patients for adverse reactions.

5.2 Hypersensitivity Reactions

Serious hypersensitivity reactions including anaphylaxis have been reported in patients treated with products containing albumin human, including DRAXIMAGE MAA [see Adverse Reactions (6)]. Obtain a history of allergy or hypersensitivity reactions. DRAXIMAGE MAA is contraindicated in patients with a history of hypersensitivity to albumin human [see Contraindications (4)] . Have emergency resuscitation equipment and trained personnel available prior to administration of Technetium Tc 99m Albumin Aggregated Injection. Monitor all patients for signs or symptoms of hypersensitivity reactions.

5.3 Risk of Temporary Impediment to Blood Flow in Patients with Right-to-Left Heart Shunts

In patients with right-to-left heart shunts, risk for temporary mechanical impediment to blood flow may exist due to the rapid entry of aggregated albumin into the systemic circulation. Administer the lowest possible number of particles of Technetium Tc 99m Albumin Aggregated Injection in these patients.

5.4 Radiation Risks

Technetium Tc 99m albumin aggregated contributes to a patient’s overall long-term cumulative radiation exposure. Long-term cumulative radiation exposure is associated with an increased risk for cancer. Ensure safe handling to minimize radiation exposure to the patient and healthcare providers. Advise patients to hydrate before and after administration and to void frequently after administration [see Dosage and Administration (2.2)].

6 ADVERSE REACTIONS

The following clinically significant adverse reactions are described elsewhere in the labeling:

- Patients with Pulmonary hypertension [see Warnings and Precautions (5.1)].
- Hypersensitivity Reactions[see Warnings and Precautions (5.2)].

The following adverse reactions associated with the use of technetium Tc 99m albumin aggregated products including DRAXIMAGE MAA were identified in clinical studies or postmarketing reports. Because these reactions are reported voluntarily from a population of uncertain size, it is not always possible to reliably estimate their frequency or establish a causal relationship to drug exposure.

Cardiovascular Disorders: Deaths in patients with severe pulmonary hypertension

Immune System Disorders: Hypersensitivity reactions such as anaphylaxis, impairment of cardiac and circulatory functions in the form of changes in respiration, pulse, and blood pressure, chest pain and syncope, urticaria, reddening of the face, sweating, and nausea

Skin and Subcutaneous Tissue Disorders: Injection site reactions

8 USE IN SPECIFIC POPULATIONS

8.1 Pregnancy

Risk Summary

Available data with Technetium Tc 99m Albumin Aggregated Injection use in pregnant women are insufficient to evaluate for a drug-associated risk of major birth defects and miscarriage. Animal reproduction studies with technetium Tc 99m albumin aggregated have not been conducted Radiopharmaceuticals have the potential to cause fetal harm depending on the fetal stage of development and the magnitude of the radiation dose. The radiation exposure to the fetus from technetium Tc 99m albumin aggregated is expected to be low (less than 0.5 mGy) (see Data).

The estimated background risk of major birth defects and miscarriage for the indicated population is unknown. All pregnancies have a background risk of birth defects, loss, or other adverse outcomes. In the U.S. general population the estimated background risk of major birth defects and miscarriage in clinically recognized pregnancies are 2% to 4% and 15% to 20%, respectively.

Data

Human Data

No adverse fetal effects of radiation risks have been identified for diagnostic procedures involving less than 50 mGy, which represents less than 10 mGy fetal doses.

8.2 Lactation

Risk Summary

Technetium-99m is present in breast milk. There are no data on the effects of technetium Tc 99m albumin aggregated on the breastfed infant or the effects on milk production. DRAXIMAGE MAA is used for imaging in infants with lung disease; exposure to technetium-99m via breastmilk is expected to be lower. Based on clinical guidelines, exposure of technetium Tc 99m albumin aggregated to a breastfed infant may be minimized by advising a lactating woman to temporarily discontinue breastfeeding and to pump and discard breast milk for a minimum of at least 24 hours after administration of Technetium Tc 99m Albumin Aggregated Injection.

The developmental and health benefits of breastfeeding should be considered along with a mother’s clinical need for DRAXIMAGE MAA, any potential adverse effects on the breastfed child from technetium Tc 99m albumin aggregated or from the underlying maternal condition.

8.4 Pediatric Use

DRAXIMAGE MAA, after radiolabeling with technetium-99m, is indicated for lung scintigraphy as an adjunct in the evaluation of pulmonary perfusion in pediatric patients (birth to less than 17 years of age). The safety profile of Technetium Tc 99m Albumin Aggregated Injection in pediatric patients is similar to adults.

The safety and efficacy of DRAXIMAGE MAA have not been established for peritoneovenous shunt scintigraphy in pediatric patients.

8.5 Geriatric Use

No formal studies of DRAXIMAGE MAA in subjects aged 65 and over were performed to determine whether they respond differently from younger adult subjects. Other reported clinical experience has not identified differences in responses between the elderly and younger adult patients. In general, dose selection for an elderly patient should be cautious; administering the low end of the particle dosing range, reflecting the greater frequency of decreased hepatic, renal, or cardiac function, and of concomitant disease or other drug therapy.

11 DESCRIPTION

11.1 Product Characteristics

DRAXIMAGE MAA contains albumin aggregated obtained by fractionating material (source blood, plasma, serum, or placentas) from healthy human donors. The macroaggregated albumin (MAA) particles are formed by denaturation of albumin human in a heating and aggregation process. Each vial contains 3,000,000 to 8,000,000 particles. By light microscopy, more than 90% of the particles are between 10 and 70 micrometers, while the typical average size is 20 to 40 micrometers; none is greater than 150 micrometers.

DRAXIMAGE MAA (kit for the preparation of technetium Tc 99m albumin aggregated) injection provides a sterile, non-pyrogenic, non-radioactive, white lyophilized powder supplied in a multiple-dose reaction vial, sealed under an atmosphere of nitrogen, for radiolabeling with Sodium Pertechnetate Tc 99m Injection to prepare Technetium Tc 99m Albumin Aggregated Injection, a radioactive diagnostic agent, for intravenous or intraperitoneal use.

Each reaction vial contains 2.5 mg of albumin aggregated, albumin human (5 mg), stannous chloride (0.06 mg minimum; 0.11 mg maximum stannous and stannic chloride) and sodium chloride (1.2 mg). Sodium hydroxide or hydrochloric acid has been added for pH adjustment. The pH is 5.2 to 6. It contains no preservative.

11.2 Physical Characteristics

Technetium-99m decays by isomeric transition with a physical half-life of 6.02 hours. The principal photon that is useful for detection and imaging studies is listed in Table 5.

Table 5. Principal Radiation Emission Data for Technetium-99m
Radiation | Mean % per Disintegration | Mean Energy (keV)
Gamma | 89.07 | 140.5

11.3 External Radiation

The specific gamma ray constant for technetium-99m is 0.78 R/mCi-hr at 1 cm. The first half value layer is 0.017 cm of lead (Pb). A range of values for the relative attenuation of the radiation resulting from the interposition of various thicknesses of lead is shown in Table 6. For example, the use of 0.25 cm thickness of lead will attenuate the radiation emitted by a factor of about 1,000.

Table 6. Radiation Attenuation by Lead Shielding
Shield Thickness (Pb) cm | Coefficient of Attenuation
0.017 | 0.5
0.08 | 10^-1
0.16 | 10^-2
0.25 | 10^-3
0.33 | 10^-4

To correct for physical decay of this radionuclide, the fractions that remain at selected intervals after the time of calibration are shown in Table 7.

Table 7. Physical Decay Chart for Technetium-99m, half-life 6.02 hours
Hours | Fraction Remaining | Hours | Fraction Remaining
0* | 1.000 | 5 | 0.562
1 | 0.891 | 6 | 0.501
2 | 0.794 | 8 | 0.398
3 | 0.708 | 10 | 0.316
4 | 0.631 | 12 | 0.251

*Calibration time

12 CLINICAL PHARMACOLOGY

12.1 Mechanism of Action

Following intravenous injection, more than 80% of the technetium Tc 99m albumin aggregated particles is trapped in the pulmonary alveolar capillary bed within 5 minutes.

Following intraperitoneal injection, technetium Tc 99m albumin aggregated mixes with the peritoneal fluid. Clearance from the peritoneal cavity varies from insignificant, which may occur with complete shunt blockage, to very rapid clearance with subsequent transfer into the systemic circulation when the shunt is patent.

12.2 Pharmacodynamics

The exposure-response relationship and time course of pharmacodynamic response for the safety and effectiveness of technetium Tc 99m albumin aggregated have not been fully characterized.

12.3 Pharmacokinetics

Distribution

Organ selectivity is a direct result of particle size. Albumin aggregated from 1 micrometer to 10 micrometers size are taken up by the reticuloendothelial system. Above 10 micrometers, the aggregates become lodged in the lung by trapping in the pulmonary alveolar capillary bed. Lung to liver ratios greater than 20:1 are obtained in the first few minutes post-injection. Distribution of particles in the lungs is a function of regional pulmonary blood flow.

The albumin aggregated is sufficiently fragile for the capillary micro-occlusion to be temporary. Erosion and fragmentation reduce the particle size, allowing passage of the aggregates through the pulmonary alveolar capillary bed. The fragments are then accumulated by the reticuloendothelial system.

Elimination

Elimination of the technetium Tc 99m albumin aggregated particles from the lungs occurs with a half-life of about 2 to 3 hours. Cumulative urinary excretion studies show an average of 20% elimination of the injected technetium Tc 99m albumin aggregated dose in 24 hours post-administration.

13 NONCLINICAL TOXICOLOGY

13.1 Carcinogenesis, Mutagenesis, Impairment of Fertility

No long term animal studies have been performed to evaluate carcinogenic potential or whether technetium Tc 99m albumin aggregated affects fertility in males or females.

16 HOW SUPPLIED/STORAGE AND HANDLING

How Supplied

DRAXIMAGE MAA (kit for the preparation of technetium Tc 99m albumin aggregated) injection contains 2.5 mg of albumin aggregated as a white lyophilized powder in a multiple-dose reaction vial, sealed under an atmosphere of nitrogen, for radiolabeling with Sodium Pertechnetate Tc 99m Injection to prepare Technetium Tc 99m Albumin Aggregated Injection. It contains no preservative.

DRAXIMAGE MAA is supplied in a carton (NDC 65174-270-30) containing 30 multiple-dose reaction vials (NDC 65174-270-01) and 30 radioassay information labels.

Storage and Handling

Before radiolabeling, store the supplied reaction vials at 2 ºC to 25ºC (36 ºF to 77 ºF).

After radiolabeling with Sodium Pertechnetate Tc 99m Injection, store Technetium Tc 99m Albumin Aggregated Injection in a lead vial shield with cap in place, refrigerated at 2 ºC to 8 ºC (36 ºF to 46 ºF) when not in use. Use within 12 hours after radiolabeling [see Dosage and Administration (2.5)].

Dispose unused Technetium Tc 99m Albumin Aggregated Injection in compliance with the appropriate regulations of the government agency authorized to license the use of this radionuclide.

This preparation is approved for use by persons under license by the Nuclear Regulatory Commission or the relevant regulatory authority of an Agreement State.

17 PATIENT COUNSELING INFORMATION

Adequate Hydration

Instruct patients to drink a sufficient amount of water to ensure adequate hydration before their imaging and urge them to drink and urinate as often as possible during the first hours following the administration of Technetium Tc 99m Aggregated Albumin Injection, in order to reduce radiation exposure[see Dosage and Administration (2.2)].

Pregnancy

Advise pregnant women of the risk of fetal exposure to radiation doses if they undergo a radionucleotide procedure [see Use in Specific Populations (8.1)].

Lactation

Advise a lactating woman to temporarily discontinue breastfeeding and to pump and discard breast milk for at least 24hours after Technetium Tc 99m Albumin Aggregated Injection administration to minimize radiation exposure to a breastfed infant [see Use in Specific Populations (8.2)].

Manufactured by:

Jubilant DraxImage Inc.

16 751 TransCanada Highway

Kirkland, Quebec H9H 4J4 Canada

1-888-633-5343

US License Number: 2186

Rev. Art: 4.0

412575

DRAXIMAGE® is a registered trademark of Jubilant DraxImage Inc.

PACKAGE LABEL.PRINCIPAL DISPLAY PANEL

MAA VIAL LABEL (INNER LABEL)

MAA CARTON

MAA POST-RECONSTITUTION LABEL